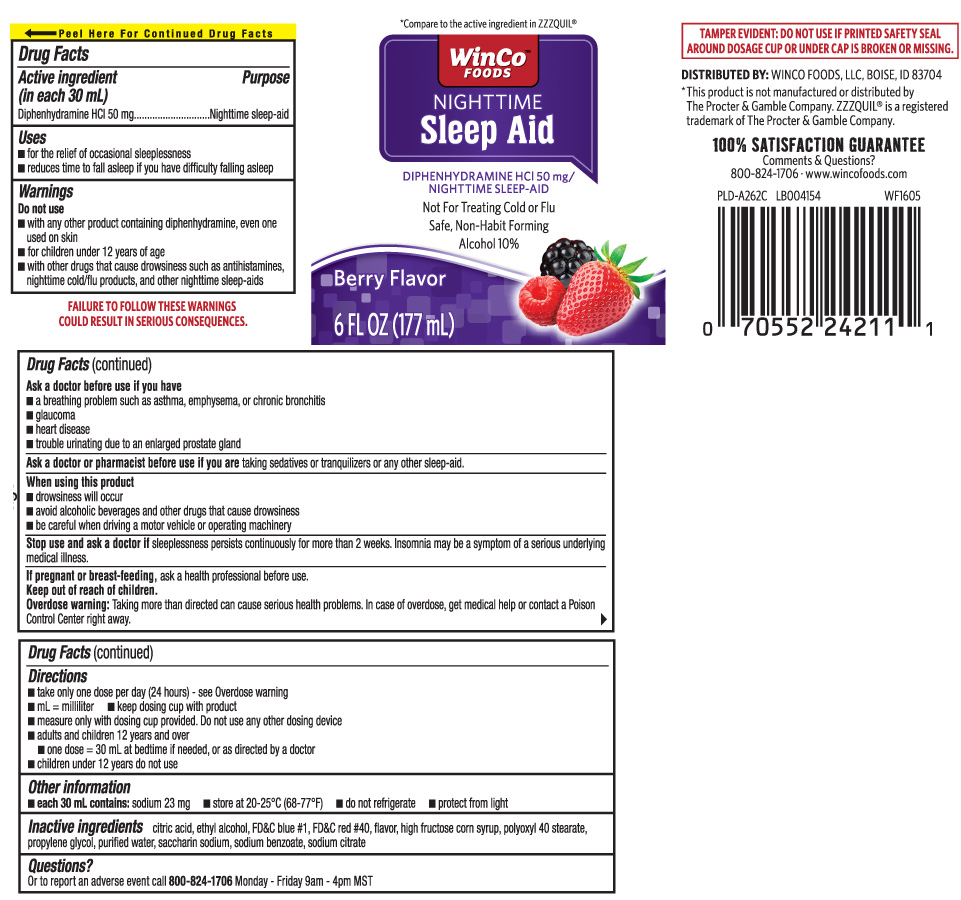 DRUG LABEL: Sleep Aid
NDC: 67091-290 | Form: LIQUID
Manufacturer: WinCo Foods, LLC
Category: otc | Type: HUMAN OTC DRUG LABEL
Date: 20240502

ACTIVE INGREDIENTS: DIPHENHYDRAMINE HYDROCHLORIDE 50 mg/30 mL
INACTIVE INGREDIENTS: ANHYDROUS CITRIC ACID; PROPYLENE GLYCOL; POLYOXYL 40 STEARATE; WATER; SODIUM BENZOATE; SACCHARIN SODIUM ANHYDROUS; TRISODIUM CITRATE DIHYDRATE; HIGH FRUCTOSE CORN SYRUP; FD&C BLUE NO. 1; ALCOHOL; FD&C RED NO. 40

Drug Facts

Active ingredient (in each 30 mL)

Diphenhydramine HCl 50 mg

Purpose

Nighttime sleep-aid

Uses

- for the relief of occasional sleeplessness
- reduces time to fall asleep if you have difficulty falling asleep

Warnings

Do not use

- with any other product containing diphenhydramine, even one used on the skin
- for children under 12 years of age
- with other drugs that cause drowsiness such as antihistamines, nighttime cold/flu products, and other nighttime sleep-aids

Ask a doctor before use if you have

- a breathing problem such as asthma, emphysema, or chronic bronchitis
- glaucoma
- heart disease
- trouble urinating due to an enlarged prostate gland

Ask a doctor or pharmacist before use if you are

taking sedatives or tranquilizers or any other sleep-aid.

When using this product

- drowsiness will occur
- avoid alcoholic beverages and other drugs that cause drowsiness
- be careful when driving a motor vehicle or operating machinery

Stop use and ask a doctor if

sleeplessness persists continuously for more than 2 weeks. Insomnia may be a symptom of serious underlying medical illness.

If pregnant or breast-feeding,

ask a health professional before use.

Keep out of reach of children.

Overdose warning: Taking more than directed can cause serious health problems. in case of overdose, get medical help or contact a Poison Control Center right away.

Directions

- take only one dose per day (24 hours) - (see overdose warning)
- mL= milliliter
- keep dosing cup with product
- measure only with dosing cup provided do not use any other dosing device
- adults and children 12 years and over
  - one dose=30 mL at bedtime if needed, or as directed by a doctor
- children under 12 years do not use

Other information

- each 30 mL contains: sodium 23 mg
- store at 20-25ºC (68-77ºF)
- do not refrigerate
- protect from light

Inactive ingredients

citric acid, ethyl alcohol, FD&C blue #1, FD&C red #40, flavor, high fructose corn syrup, polyoxyl 40 stearate, propylene glycol, purified water, saccharin sodium , sodium benzoate, trisodium citrate dihydrate

Questions?

Or to report an adverse event call 800-824-1706 Monday - Friday 9am - 4PM MST

Principal Display Panel

*Compare to the active igredient in ZZZQUIL®

NIGHTTIME

Sleep Aid

DIPHENHYDRAMINE HCI 50 mg / NIGHTTIME SLEEP-AID

Not For Treating Cold or Flu

Safe, Non-Habit Forming

Alcohol 10%

Berry Flavor

FL OZ (mL)

FAILURE TO FOLLOW THESE WARNINGS COULD RESULT IN SERIOUS CONSEQUENCES

TAMPER EVIDENT: DO NOT USE IF PRINTED SAFETY SEAL AROUND DOSAGE CUP OR UNDER CAP IS BROKEN OR MISSING.

*This product is not manufactured or distributed byThe Procter & Gamble Company. ZZZQUIL® is a registered trademark of The Procter & Gamble Company.

DISTRIBUTED BY: WINCO FOODS, LLC, BOISE, ID 83704

www.wincofoods.com

Package Label

Winco Foods NightTime Sleep-Aid Berry Flavor